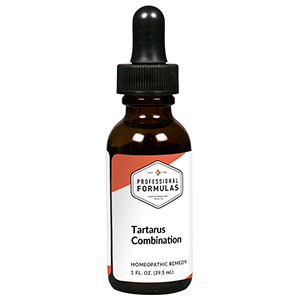 DRUG LABEL: Tartarus Combination
NDC: 63083-9259 | Form: LIQUID
Manufacturer: Professional Complementary Health Formulas
Category: homeopathic | Type: HUMAN OTC DRUG LABEL
Date: 20190815

ACTIVE INGREDIENTS: STACHYS OFFICINALIS 2 [hp_X]/29.5 mL; ANISE 3 [hp_X]/29.5 mL; EPHEDRA DISTACHYA FLOWERING TWIG 3 [hp_X]/29.5 mL; ANEMONE HEPATICA VAR. OBTUSA 3 [hp_X]/29.5 mL; AMARYLLIS BELLADONNA WHOLE 4 [hp_X]/29.5 mL; IPECAC 4 [hp_X]/29.5 mL; LOBELIA INFLATA WHOLE 4 [hp_X]/29.5 mL; SODIUM SULFATE 4 [hp_X]/29.5 mL; ASPIDOSPERMA QUEBRACHO-BLANCO ROOT 5 [hp_X]/29.5 mL; ANTIMONY POTASSIUM TARTRATE 6 [hp_X]/29.5 mL; ARSENIC TRIIODIDE 6 [hp_X]/29.5 mL; BLATTA ORIENTALIS 6 [hp_X]/29.5 mL; NAPHTHALENE 6 [hp_X]/29.5 mL; GONORRHEAL URETHRAL SECRETION HUMAN 12 [hp_X]/29.5 mL; BOVINE TUBERCULIN 12 [hp_X]/29.5 mL
INACTIVE INGREDIENTS: ALCOHOL; WATER

R259

ACTIVE INGREDIENTS

Stachys betonica 2X
Anisum 3X
Ephedra vulgaris 3X
Hepatica triloba 3X
Belladonna 4X
Ipecacuanha 4X
Lobelia inflata 4X
Natrum sulphuricum 4X
Quebracho 5X
Antimonium tartaricum 6X
Arsenicum iodatum 6X
Blatta orientalis 6X
Naphthalinum 6X
Medorrhinum 12X
Tuberculinum 12X

QUESTIONS

Professional Formulas

PO Box 2034 Lake Oswego, OR 97035

INDICATIONS

For the temporary relief of coughing, wheezing, nasal or bronchial congestion.*

PURPOSE

*Claims based on traditional homeopathic practice, not accepted medical evidence. Not FDA evaluated.

WARNINGS

If symptoms do not improve or are accompanied by a fever, consult a doctor. Keep out of the reach of children. In case of overdose, get medical help or contact a poison control center right away. If pregnant or breastfeeding, ask a healthcare professional before use.

Keep out of the reach of children.

PREGNANCY OR BREAST FEEDING

If pregnant or breastfeeding, ask a healthcare professional before use.

DIRECTIONS

Place drops under tongue 30 minutes before/after meals. Adults and children 12 years and over: Take 10 drops up to 3 times per day. Consult a physician for use in children under 12 years of age.

OTHER INFORMATION

Tamper resistant. If seal is broken, do not use. After opening, close container tightly and store at room temperature away from heat.

INACTIVE INGREDIENTS

40% ethanol, purified water.

LABEL

Est 1985

Professional Formulas

Complementary Health

Tartarus Combination

Homeopathic Remedy

1 FL. OZ. (29.5 mL)